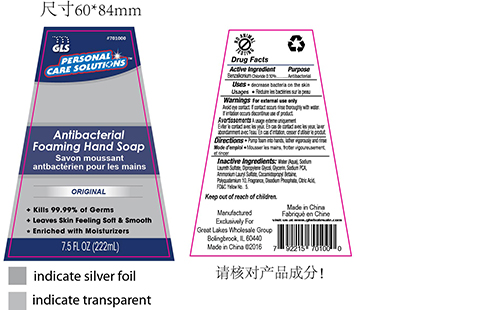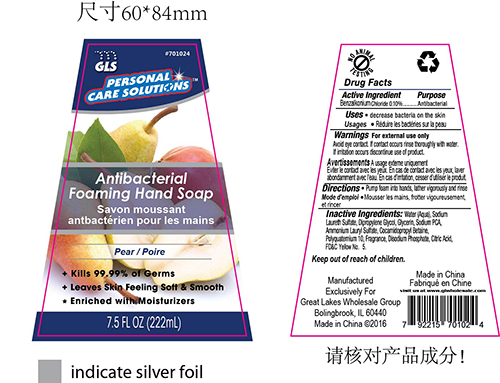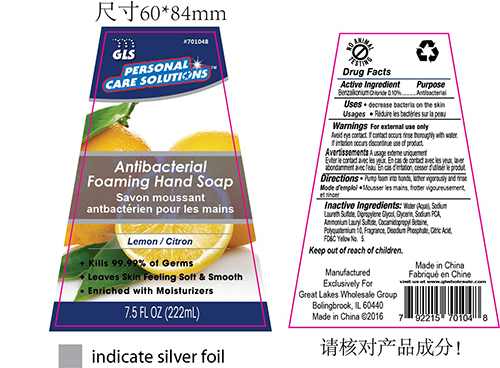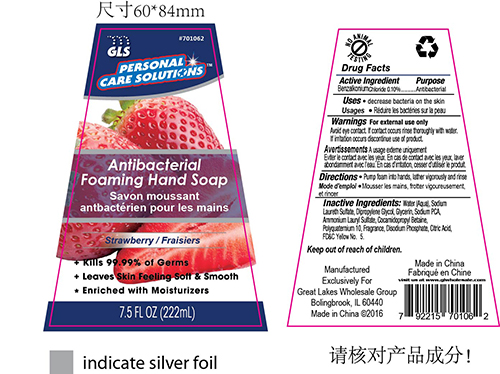 DRUG LABEL: Hand wash
NDC: 64092-362 | Form: LIQUID
Manufacturer: Great Lakes Wholesale, Marketing, and Sales, Inc
Category: otc | Type: HUMAN OTC DRUG LABEL
Date: 20160829

ACTIVE INGREDIENTS: BENZALKONIUM CHLORIDE 0.222 g/222 mL
INACTIVE INGREDIENTS: WATER

DESCRIPTION

GLS PERSONAL CARE SOLUTIONS

Antibacterial Foaming Hand Soap

Kills 99.99% of Germs

Leaves Skin Feeling Soft & Smooth

Enriched with Moisturizers

7.5 fl oz (222mL)

Active Ingredient Purpose

Benzalkonium Chloride 0.10% ...........................Antibacterial

PURPOSE

Hand Soap

INDICATIONS AND USAGE

Decrease bacteria on the skin.

WARNINGS

For external use only

Avoid eye contact. If contact occurs rinse thoroughly with water.

INSTRUCTIONS FOR USE

Pump foam into hands, lather vigorously and rinse.

DOSAGE AND ADMINISTRATION

Antibacterial Foaming Hand Soap

0.10% Benzalkonium Chloride

INACTIVE INGREDIENT

Water (Aqua), Sodium Laureth Sulfate, Dipropylene Glycol, Glycerin, Sodium PCA, Ammonium Lauryl Sulfate, Cocamidopropyl Betaine, Polyquatemium 10, Fragrance, Disodium Phosphate, Citric Acid, FD&C Yellow No. 5.